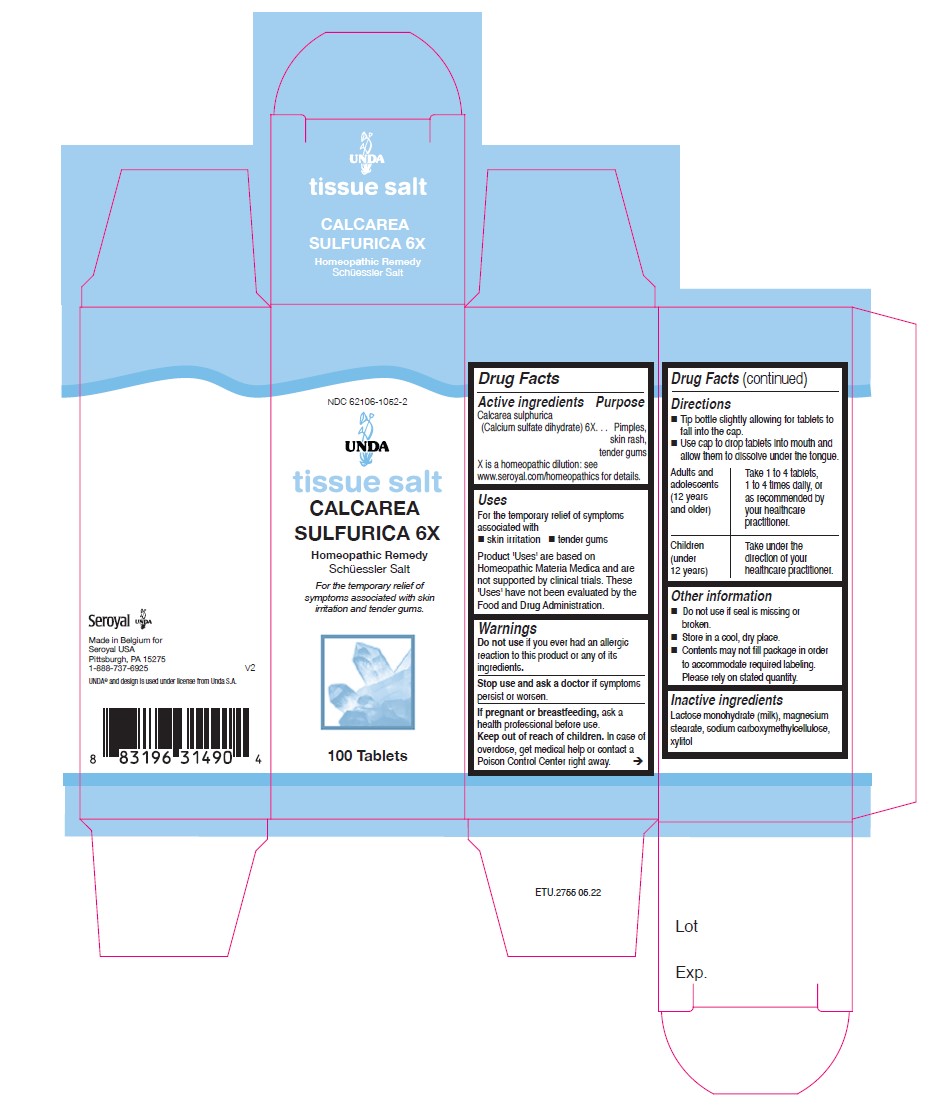 DRUG LABEL: CALCAREA SULFURICA 6X
NDC: 62106-1052 | Form: TABLET
Manufacturer: Seroyal USA
Category: homeopathic | Type: HUMAN OTC DRUG LABEL
Date: 20220707

ACTIVE INGREDIENTS: CALCIUM SULFATE ANHYDROUS 6 [hp_X]/1 1
INACTIVE INGREDIENTS: MAGNESIUM STEARATE; LACTOSE MONOHYDRATE; CARBOXYMETHYLCELLULOSE SODIUM; XYLITOL

CALCAREA SULFURICA 6X

Active ingredients
Calcarea sulphurica (Calcium sulfate) 6X

PURPOSE

For the temporary relief of symptoms associated with

skin irritation

tender gums

Warnings
Do not use if you ever had an allergic
reaction to this product or any of its
ingredients.
Stop use and ask a doctor if symptoms
persist or worsen.
If pregnant or breastfeeding, ask a
health professional before use.
Keep out of reach of children. In case of
overdose, get medical help or contact a
Poison Control Center right away.

Keep out of reach of children. In case of
overdose, get medical help or contact a
Poison Control Center right away

PREGNANCY OR BREAST FEEDING

If pregnant or breastfeeding, ask a
health professional before use.

Other information
Do not use if seal is missing or broken.
Store in a cool, dry place.

Inactive ingredients
Lactose monohydrate (milk), magnesium
stearate, sodium carboxymethylcellulose,
xylitol

Directions
Tip bottle slightly allowing for tablets to fall into the cap.
Use cap to drop tablets into mouth and allow them to dissolve under the tongue.
Adults and adolescents (12 years and older)

Take 1 to 4 tablets, one to four times daily, or as recommended by your healthcare practitioner.
Children (under 12 years)
Take under the direction of your healthcare practitioner.

Uses
For the temporary relief of symptoms associated with

skin irritation

tender gums

Directions
Tip bottle slightly allowing for tablets to fall into the cap.
Use cap to drop tablets into mouth and allow them to dissolve under the tongue.
Adults and adolescents (12 years and older)

Take 1 to 4 tablets, one to four times daily, or as recommended by your healthcare practitioner.
Children (under 12 years)
Take under the direction of your healthcare practitioner.

PACKAGE LABEL

UNDA

tissue salt

CALCAREA SULFURICA 6X

Homeopathic Remedy

Schuessler Salt

For the temporary relief of symptoms associated with skin irritation and tender gum.

100 Tablets